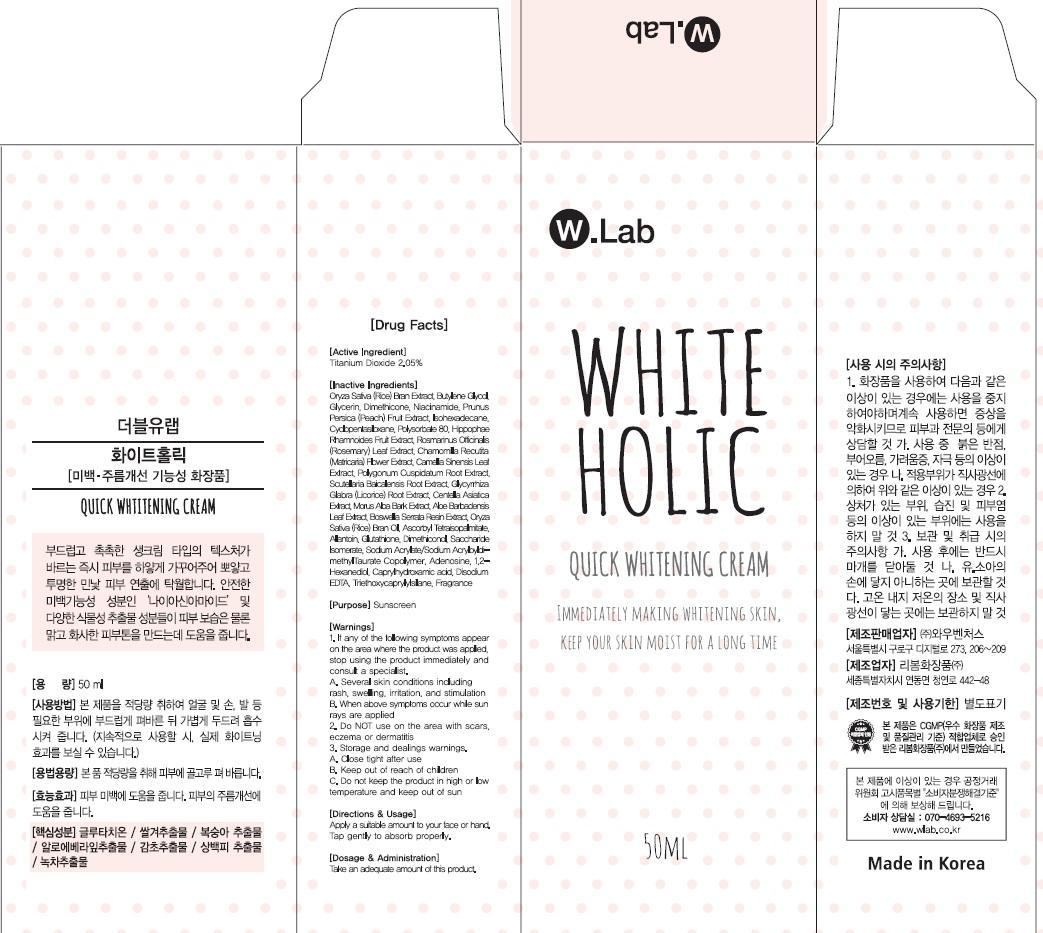 DRUG LABEL: White Holic 50mL
NDC: 69894-060 | Form: CREAM
Manufacturer: WOW VENTURES
Category: otc | Type: HUMAN OTC DRUG LABEL
Date: 20181228

ACTIVE INGREDIENTS: Titanium Dioxide 1.02 mg/50 mL
INACTIVE INGREDIENTS: Butylene Glycol; Glycerin

ACTIVE INGREDIENT

Active Ingredient: Titanium Dioxide 2.05%

INACTIVE INGREDIENT

Inactive Ingredients: Oryza Sativa (Rice) Bran Extract, Butylene Glycol, Glycerin, Dimethicone, Niacinamide, Prunus Persica (Peach) Fruit Extract, Isohexadecane, Cyclopentasiloxane, Polysorbate 80, Hippophae Rhamnoides Fruit Extract, Rosmarinus Officinalis (Rosemary) Leaf Extract, Chamomilla Recutita (Matricaria) Flower Extract, Camellia Sinensis Leaf Extract, Polygonum Cuspidatum Root Extract, Scutellaria Baicalensis Root Extract, Glycyrrhiza Glabra (Licorice) Root Extract, Centella Asiatica Extract, Morus Alba Bark Extract, Aloe Barbadensis Leaf Extract, Boswellia Serrata Resin Extract, Oryza Sativa (Rice) Bran Oil, Ascorbyl Tetraisopalmitate, Allantoin, Glutathione, Dimethiconol, Saccharide Isomerate, Sodium Acrylate/Sodium AcryloyldimethylTaurate Copolymer, Adenosine, 1,2-Hexanediol, Caprylhydroxamic acid, Disodium EDTA, Triethoxycaprylylsilane, Fragrance

PURPOSE

Purpose: Sunscreen

WARNINGS

Warnings: 1. If any of the following symptoms appear on the area where the product was applied, stop using the product immediately and consult a specialist. A. Several skin conditions including rash, swelling, irritation, and stimulation B. When above symptoms occur while sun rays are applied 2. Do NOT use on the area with scars, eczema or dermatitis 3. Storage and dealings warnings. A. Close tight after use B. Keep out of reach of children C. Do not keep the product in high or low temperature and keep out of sun

DESCRIPTION

Directions & Usage: Apply a suitable amount to your face or hand. Tap gently to absorb properly.

Dosage & Administration: Take an adequate amount of this product.